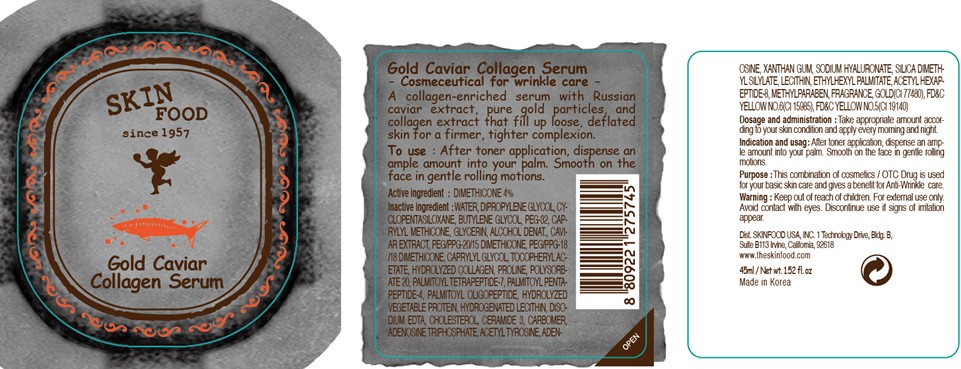 DRUG LABEL: GOLD CAVIAR COLLAGEN SERUM
NDC: 76214-001 | Form: CREAM
Manufacturer: SKINFOOD CO., LTD.
Category: otc | Type: HUMAN OTC DRUG LABEL
Date: 20110714

ACTIVE INGREDIENTS: DIMETHICONE 1.8 mL/45 mL
INACTIVE INGREDIENTS: WATER; DIPROPYLENE GLYCOL; CYCLOMETHICONE 5; BUTYLENE GLYCOL; POLYETHYLENE GLYCOL 1500; GLYCERIN; CAVIAR; CAPRYLYL GLYCOL; PROLINE; POLYSORBATE 20; PALMITOYL TETRAPEPTIDE-7; PALMITOYL PENTAPEPTIDE-4; PALMITOYL OLIGOPEPTIDE; METHYLPARABEN; HYDROGENATED SOYBEAN LECITHIN; EDETATE DISODIUM; CHOLESTEROL; CERAMIDE 3; ADENOSINE TRIPHOSPHATE; GOLD; ADENOSINE; XANTHAN GUM; LECITHIN, SOYBEAN; ETHYLHEXYL PALMITATE

Drug Facts

Active ingredient: DIMETHICONE

Inactive ingredients:

WATER, DIPROPYLENE GLYCOL, CYCLOPENTASILOXANE, BUTYLENE GLYCOL, PEG-32, CAPRYLYL METHICONE, GLYCERIN, ALCOHOL DENAT., CAVIAR EXTRACT, PEG/PPG-20/15 DIMETHICONE, PEG/PPG-18/18 DIMETHICONE, CAPRYLYL GLYCOL, TOCOPHERYL ACETATE, HYDROLYZED COLLAGEN, PROLINE, POLYSORBATE 20, PALMITOYL TETRAPEPTIDE-7, PALMITOYL PENTAPEPTIDE-4, PALMITOYL OLIGOPEPTIDE, HYDROLYZED VEGETABLE PROTEIN, HYDROGENATED LECITHIN, DISODIUM EDTA, CHOLESTEROL, CERAMIDE 3, CARBOMER, ADENOSINE TRIPHOSPHATE, ACETYL TYROSINE, ADENOSINE, XANTHAN GUM, SODIUM HYALURONATE, SILICA DIMETHYL SILYLATE, LECITHIN, ETHYLHEXYL PALMITATE, ACETYL HEXAPEPTIDE-8, METHYLPARABEN, FRAGRANCE, GOLD, CI 15985, CI 19140

Purpose:

This combination of cosmetics is used for your basic skin care and gives a benefit for Anti-Wrinkle care.

Warnings:

For external use only. Avoid contact with eyes. Discontinue use if signs of irritation appear.

Keep out of reach of children:

Keep out of reach of children.

Indication and usage:

After toner application, dispense an ample amount into your palm. Smooth on the face in gentle rolling motions.

Dosage and administration:

Take appropriate amount according to your skin condition and apply every morning and night.